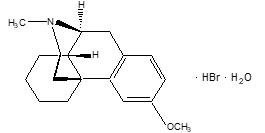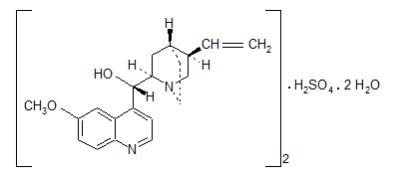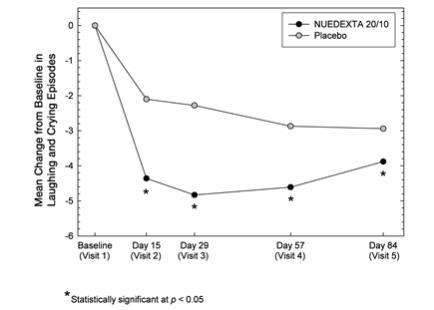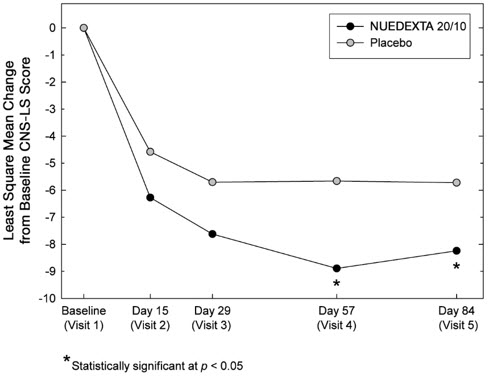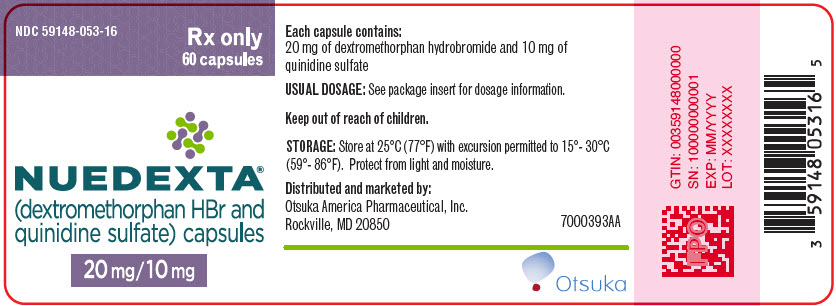 DRUG LABEL: Nuedexta
NDC: 59148-053 | Form: CAPSULE, GELATIN COATED
Manufacturer: Otsuka America Pharmaceutical, Inc
Category: prescription | Type: HUMAN PRESCRIPTION DRUG LABEL
Date: 20260122

ACTIVE INGREDIENTS: dextromethorphan hydrobromide 20 mg/1 1; QUINIDINE SULFATE 10 mg/1 1

HIGHLIGHTS OF PRESCRIBING INFORMATION

These highlights do not include all the information needed to use NUEDEXTA safely and effectively. See full prescribing information for NUEDEXTA.
NUEDEXTA (dextromethorphan hydrobromide and quinidine sulfate) capsules, for oral use
Initial U.S. Approval: 2010

1 INDICATIONS AND USAGE

NUEDEXTA is a combination product containing dextromethorphan hydrobromide (an uncompetitive NMDA receptor antagonist and sigma-1 agonist) and quinidine sulfate (a CYP450 2D6 inhibitor) indicated for the treatment of pseudobulbar affect (PBA). (1)

2 DOSAGE AND ADMINISTRATION

- Starting dose: one capsule daily by mouth for 7 days. (2.1)
- Maintenance dose: After 7 days, 1 capsule every 12 hours. (2.1)

3 DOSAGE FORMS AND STRENGTHS

Capsules: Dextromethorphan hydrobromide 20 mg/quinidine sulfate 10 mg. (3)

4 CONTRAINDICATIONS

- Concomitant use with quinidine, quinine, or mefloquine. (4.1)
- Patients with a history of quinidine, quinine or mefloquine-induced thrombocytopenia, hepatitis, or other hypersensitivity reactions. (4.2)
- Patients with known hypersensitivity to dextromethorphan. (4.2)
- Use with an MAOI or within 14 days of stopping an MAOI. Allow 14 days after stopping NUEDEXTA before starting an MAOI. (4.3)
- Prolonged QT interval, congenital long QT syndrome, history suggestive of torsades de pointes, or heart failure. (4.4)
- Complete atrioventricular (AV) block without implanted pacemaker, or patients at high risk of complete AV block. (4.4)
- Concomitant use with drugs that both prolong QT interval and are metabolized by CYP2D6 (e.g., thioridazine or pimozide). (4.4)

5 WARNINGS AND PRECAUTIONS

- Thrombocytopenia or other hypersensitivity reactions: Discontinue if occurs. (5.1)
- Hepatitis: Discontinue if occurs. (5.2)
- QT Prolongation: Monitor ECG if concomitant use of drugs that prolong QT interval cannot be avoided or if concomitant CYP3A4 inhibitors used. (5.3)

- Left ventricular hypertrophy (LVH) or left ventricular dysfunction (LVD): Monitor ECG in patients with LVH or LVD. (5.3)
- CYP2D6 substrate: Nuedexta inhibits CYP2D6. Accumulation of parent drug and/or failure of metabolite formation may decrease safety and/or efficacy of concomitant CYP2D6 metabolized drugs. Adjust dose of CYP2D6 substrate or use alternative treatment when clinically indicated. (5.4, 12.4)
- Dizziness: Take precautions to reduce falls. (5.5)
- Serotonin syndrome: Use of NUEDEXTA with selective serotonin reuptake inhibitor (SSRIs) or tricyclic antidepressants increases the risk. Discontinue if occurs. (5.6, 7.4)
- Anticholinergic effects of quinidine: Monitor for worsening in myasthenia gravis and other sensitive conditions. (5.7)

6 ADVERSE REACTIONS

The most common adverse reactions (incidence of ≥3% and two-fold greater than placebo) in patients taking NUEDEXTA are diarrhea, dizziness, cough, vomiting, asthenia, peripheral edema, urinary tract infection, influenza, increased gamma-glutamyltransferase, and flatulence. (6.1)

To report SUSPECTED ADVERSE REACTIONS, contact Otsuka America Pharmaceutical, Inc. at 1-800-438-9927 or FDA at 1-800-FDA-1088 or www.fda.gov/medwatch.

7 DRUG INTERACTIONS

- Desipramine: Exposure increases 8-fold. Reduce desipramine dose and adjust based on clinical response. (7.5, 12.4)
- Paroxetine: Exposure increases 2-fold. Reduce paroxetine dose and adjust based on clinical response. (7.5, 12.4)
- Digoxin: Increased digoxin substrate plasma concentration may occur. (7.6)

8 USE IN SPECIFIC POPULATIONS

- Pregnancy: Based on animal data, may cause fetal harm. (8.1)

FULL PRESCRIBING INFORMATION

1 INDICATIONS AND USAGE

NUEDEXTA is indicated for the treatment of pseudobulbar affect (PBA).

PBA occurs secondary to a variety of otherwise unrelated neurologic conditions, and is characterized by involuntary, sudden, and frequent episodes of laughing and/or crying. PBA episodes typically occur out of proportion or incongruent to the underlying emotional state. PBA is a specific condition, distinct from other types of emotional lability that may occur in patients with neurological disease or injury.

2 DOSAGE AND ADMINISTRATION

2.1 Recommended Dose

The recommended starting dose of NUEDEXTA is one capsule daily by mouth for the initial seven days of therapy. On the eighth day of therapy and thereafter, the daily dose should be a total of two capsules a day, given as one capsule every 12 hours.

The need for continued treatment should be reassessed periodically, as spontaneous improvement of PBA occurs in some patients.

3 DOSAGE FORMS AND STRENGTHS

NUEDEXTA capsules contain 20 mg dextromethorphan hydrobromide and 10 mg quinidine sulfate in a brick red gelatin capsule with "DMQ 20-10" printed in white ink on the capsule.

4 CONTRAINDICATIONS

4.1 Quinidine and Related Drugs

NUEDEXTA contains quinidine and should not be used concomitantly with other drugs containing quinidine, quinine, or mefloquine.

4.2 Hypersensitivity

NUEDEXTA is contraindicated in patients with a history of NUEDEXTA, quinine, mefloquine or quinidine-induced thrombocytopenia, hepatitis, bone marrow depression or lupus-like syndrome. NUEDEXTA is also contraindicated in patients with a known hypersensitivity to dextromethorphan (e.g., rash, hives) [see Warnings and Precautions (5.1)].

4.3 MAOIs

NUEDEXTA is contraindicated in patients taking monoamine oxidase inhibitors (MAOIs) or in patients who have taken MAOIs within the preceding 14 days, due to the risk of serious and possibly fatal drug interactions, including serotonin syndrome. Allow at least 14 days after stopping NUEDEXTA before starting an MAOI [see Drug Interactions (7.1)].

4.4 Cardiovascular

NUEDEXTA is contraindicated in patients with a prolonged QT interval, congenital long QT syndrome or a history suggestive of torsades de pointes, and in patients with heart failure [see Warnings and Precautions (5.3)].

NUEDEXTA is contraindicated in patients receiving drugs that both prolong QT interval and are metabolized by CYP2D6 (e.g., thioridazine and pimozide), as effects on QT interval may be increased [see Drug Interactions (7.2)].

NUEDEXTA is contraindicated in patients with complete atrioventricular (AV) block without implanted pacemakers, or in patients who are at high risk of complete AV block.

5 WARNINGS AND PRECAUTIONS

5.1 Thrombocytopenia and Other Hypersensitivity Reactions

Quinidine can cause immune-mediated thrombocytopenia that can be severe or fatal. Non-specific symptoms, such as lightheadedness, chills, fever, nausea, and vomiting, can precede or occur with thrombocytopenia. NUEDEXTA should be discontinued immediately if thrombocytopenia occurs, unless the thrombocytopenia is clearly not drug-related, as continued use increases the risk for fatal hemorrhage. Likewise, NUEDEXTA should not be restarted in sensitized patients, because more rapid and more severe thrombocytopenia than the original episode can occur. NUEDEXTA should not be used if immune-mediated thrombocytopenia from structurally related drugs, including quinine and mefloquine is suspected, as cross-sensitivity can occur. Quinidine-associated thrombocytopenia usually, but not always, resolves within a few days of discontinuation of the sensitizing drug.

Quinidine has also been associated with a lupus-like syndrome involving polyarthritis, sometimes with a positive antinuclear antibody test. Other associations include rash, bronchospasm, lymphadenopathy, hemolytic anemia, vasculitis, uveitis, angioedema, agranulocytosis, the sicca syndrome, myalgia, elevation in serum levels of skeletal-muscle enzymes, and pneumonitis.

5.2 Hepatotoxicity

Hepatitis, including granulomatous hepatitis, has been reported in patients receiving quinidine, generally during the first few weeks of therapy. Fever may be a presenting symptom, and thrombocytopenia or other signs of hypersensitivity may also occur. Most cases remit when quinidine is withdrawn.

5.3 Cardiac Effects

NUEDEXTA causes dose-dependent QTc prolongation [see Clinical Pharmacology (12.2)]. QT prolongation can cause torsades de pointes-type ventricular tachycardia, with the risk increasing as the degree of prolongation increases. When initiating NUEDEXTA in patients at risk of QT prolongation and torsades de pointes, electrocardiographic (ECG) evaluation of QT interval should be conducted at baseline and 3 to 4 hours after the first dose. This includes patients concomitantly taking/initiating drugs that prolong the QT interval or that are strong or moderate CYP3A4 inhibitors, and patients with left ventricular hypertrophy (LVH) or left ventricular dysfunction (LVD). LVH and LVD are more likely to be present in patients with chronic hypertension, known coronary artery disease, or history of stroke. LVH and LVD can be diagnosed utilizing echocardiography or another suitable cardiac imaging modality.

Strong and moderate CYP3A inhibitors include, but are not limited to, atazanavir, clarithromycin, indinavir, itraconazole, ketoconazole, nefazodone, nelfinavir, ritonavir, saquinavir, telithromycin, amprenavir, aprepitant, diltiazem, erythromycin, fluconazole, fosamprenavir, grapefruit juice, and verapamil.

Reevaluate ECG if risk factors for arrhythmia change during the course of treatment with NUEDEXTA. Risk factors include concomitant use of drugs associated with QT prolongation, electrolyte abnormality (hypokalemia, hypomagnesemia), bradycardia, and family history of QT abnormality. Hypokalemia and hypomagnesemia should be corrected prior to initiation of therapy with NUEDEXTA, and should be monitored during treatment.

If patients taking NUEDEXTA experience symptoms that could indicate the occurrence of cardiac arrhythmias, e.g., syncope or palpitations, NUEDEXTA should be discontinued and the patient further evaluated.

5.4 Concomitant use of CYP2D6 Substrates

The quinidine in NUEDEXTA inhibits CYP2D6 in patients in whom CYP2D6 is not otherwise genetically absent or its activity otherwise pharmacologically inhibited [see Warnings and Precautions (5.8) and Clinical Pharmacology (12.3, 12.5)]. Because of this effect on CYP2D6, accumulation of parent drug and/or failure of active metabolite formation may decrease the safety and/or the efficacy of drugs used concomitantly with NUEDEXTA that are metabolized by CYP2D6 [see Drug Interactions (7.5)].

5.5 Dizziness

NUEDEXTA may cause dizziness [see Adverse Reactions (6.1)]. Precautions to reduce the risk of falls should be taken, particularly for patients with motor impairment affecting gait or a history of falls. In a controlled trial of NUEDEXTA, 10% of patients on NUEDEXTA and 5% on placebo experienced dizziness.

5.6 Serotonin Syndrome

When used with SSRIs (such as fluoxetine) or tricyclic antidepressants (such as clomipramine and imipramine), NUEDEXTA may cause "serotonin syndrome", with changes including altered mental status, hypertension, restlessness, myoclonus, hyperthermia, hyperreflexia, diaphoresis, shivering, and tremor [see Drug Interactions (7.4), Overdosage (10)].

5.7 Anticholinergic Effects of Quinidine

Monitor for worsening clinical condition in myasthenia gravis and other conditions that may be adversely affected by anticholinergic effects.

5.8 CYP2D6 Poor Metabolizers

The quinidine component of NUEDEXTA is intended to inhibit CYP2D6 so that higher exposure to dextromethorphan can be achieved compared to when dextromethorphan is given alone [see Warnings and Precautions (5.4) and Clinical Pharmacology (12.3, 12.5)]. Approximately 7 to 10% of Caucasians and 3 to 8% of African Americans lack the capacity to metabolize CYP2D6 substrates and are classified as poor metabolizers (PMs). The quinidine component of NUEDEXTA is not expected to contribute to the effectiveness of NUEDEXTA in PMs, but adverse events of the quinidine are still possible. In those patients who may be at risk of significant toxicity due to quinidine, genotyping to determine if they are PMs should be considered prior to making the decision to treat with NUEDEXTA.

6 ADVERSE REACTIONS

A total of 946 patients participated in four Phase 3 controlled and uncontrolled PBA studies and received at least one dose of the combination product of dextromethorphan/quinidine in various strengths at the recommended or higher than the recommended dose. Of those patients, 393 patients were exposed for at least 180 days and 294 patients were exposed for at least one year. Median exposure was 168 days.

Controlled trials enrolled only patients with either ALS or MS. Uncontrolled studies enrolled 136 patients with PBA secondary to a wide variety of underlying neurological conditions including stroke (45 patients) and traumatic brain injury (23 patients). Consequently, patients with other underlying neurologic diseases may experience other adverse reactions not described below.

6.1 Clinical Trials Experience

A 12-week, placebo-controlled study evaluated NUEDEXTA (dextromethorphan 20 mg/quinidine 10 mg) (N=107) and a 30 mg dextromethorphan/10 mg quinidine combination (N=110) compared to placebo (N=109). Approximately 60% of patients had ALS and 40% had MS. Patients were 25 to 80 years of age, with a mean age of approximately 51 years. Three (3) ALS patients in each drug treatment arm and 1 ALS patient in the placebo arm died during the 12-week placebo-control period. All deaths were consistent with the natural progression of ALS.

Adverse Reactions Leading to Discontinuation

The most commonly reported adverse reactions (incidence ≥2% and greater than placebo) that led to discontinuation with the 20 mg dextromethorphan/10 mg quinidine twice daily dose were muscle spasticity (3%), respiratory failure (1%), abdominal pain (2%), asthenia (2%), dizziness (2%), fall (1%), and muscle spasms (2%).

Most Common Adverse Reactions

Adverse drug reactions that occurred in ≥3% of patients receiving the 20 mg dextromethorphan/10 mg quinidine twice daily dose, and at an incidence of ≥2 times placebo in short-term clinical trials in ALS and MS are provided in Table 1. Because clinical trials are conducted under widely varying conditions, adverse reaction rates observed in the clinical trials of a drug cannot be directly compared to the rates in the clinical trials of another drug and may not reflect the rates observed in clinical practice.

Table 1: Adverse Drug Reactions with an Incidence of ≥3% of Patients and ≥2× Placebo in NUEDEXTA-treated Patients by System-Organ Class and Preferred Term
 | NUEDEXTA N=107 % | Placebo N=109 %
Diarrhea | 13 | 6
Dizziness | 10 | 5
Cough | 5 | 2
Vomiting | 5 | 1
Asthenia | 5 | 2
Peripheral edema | 5 | 1
Urinary tract infection | 4 | 1
Influenza | 4 | 1
Increased gamma-glutamyltransferase | 3 | 0
Flatulence | 3 | 1

6.2 Long-Term Exposure with NUEDEXTA

The experience in open-label clinical trials is consistent with the safety profile observed in the placebo-controlled clinical trials.

6.3 Safety Experience of Individual Components

The following adverse reactions have been reported with the use of the individual components of NUEDEXTA, dextromethorphan and quinidine, from post-marketing experience. Because these reactions are reported voluntarily from a population of unknown size, it is not always possible to reliably estimate their frequency or establish a causal relationship to drug exposure.

Dextromethorphan

Drowsiness, dizziness, nervousness or restlessness, nausea, vomiting, and stomach pain.

Quinidine

Cinchonism is most often a sign of chronic quinidine toxicity, but it may appear in sensitive patients after a single moderate dose of several hundred milligrams. Cinchonism is characterized by nausea, vomiting, diarrhea, headache tinnitus, hearing loss, vertigo, blurred vision, diplopia, photophobia, confusion, and delirium.

Convulsions, apprehension, and ataxia have been reported with quinidine therapy, but it is not clear that these were not simply the results of hypotension and consequent cerebral hypoperfusion in patients being treated for cardiovascular indications. Acute psychotic reactions have been reported to follow the first dose of quinidine, but these reactions appear to be extremely rare. Other adverse reactions occasionally reported with quinidine therapy include depression, mydriasis, disturbed color perception, night blindness, scotomata, optic neuritis, visual field loss, photosensitivity, keratopathy, and abnormalities of skin pigmentation.

7 DRUG INTERACTIONS

7.1 MAOIs

Do not use NUEDEXTA with monoamine oxidase inhibitors (MAOIs) or in patients who have taken MAOIs within the preceding 14 days [see Contraindications (4.3)].

7.2 Drugs that Prolong QT and are Metabolized by CYP2D6

Do not use with drugs that both prolong QT interval and are metabolized by CYP2D6 (e.g., thioridazine or pimozide) [see Contraindications (4.4)].

7.3 Drugs that Prolong QT and Concomitant CYP3A4 Inhibitors

Recommend ECG in patients taking drugs with NUEDEXTA that prolong the QT interval and in patients taking concomitant moderate or strong CYP3A4 inhibitors [see Warnings and Precautions (5.3)].

7.4 SSRIs and Tricyclic Antidepressants

Use of NUEDEXTA with SSRIs or tricyclic antidepressants increases the risk of 'serotonin syndrome' [see Warnings and Precautions (5.6)].

7.5 CYP2D6 Substrate

The co-administration of NUEDEXTA with drugs that undergo extensive CYP2D6 metabolism may result in altered drug effects, due to accumulation of parent drug and/or failure of metabolite formation [see Warnings and Precautions (5.4)]. Therapy with medications that are primarily metabolized by CYP2D6 and that have a relatively narrow therapeutic index should be initiated at a low dose if a patient is receiving NUEDEXTA concurrently. If NUEDEXTA is added to the treatment regimen of a patient already receiving a drug primarily metabolized by CYP2D6, the need for a dose modification of the original medication should be considered. The extent to which CYP2D6 interactions may pose clinical problems will depend on the pharmacokinetics of the substrate involved.

In cases of prodrugs whose actions are mediated by the CYP2D6-produced metabolites (for example, codeine and hydrocodone, whose analgesic and antitussive effects appear to be mediated by morphine and hydromorphone, respectively), it may not be possible to achieve the desired clinical benefits in the presence of NUEDEXTA due to quinidine-mediated inhibition of CYP2D6. Consider use of alternative treatment with NUEDEXTA when clinically indicated.

Drug interactions with desipramine and paroxetine have been studied in controlled clinical trials with a higher dose combination of dextromethorphan/quinidine (dextromethorphan 30 mg/quinidine 30 mg) than NUEDEXTA; study results are described below. No other drug interactions with CYP2D6 substrates have been systematically investigated, although concomitant use of such drugs was allowed in clinical trials with NUEDEXTA and in clinical trials with higher dose formulations of dextromethorphan/quinidine.

Desipramine (CYP2D6 substrate):

The tricyclic antidepressant desipramine is metabolized primarily by CYP2D6. A drug interaction study was conducted between a higher combination dose of dextromethorphan (dextromethorphan 30 mg/quinidine 30 mg) and desipramine 25 mg. The combination dose of dextromethorphan/quinidine increased steady state desipramine levels approximately 8-fold. If NUEDEXTA and desipramine are prescribed concomitantly, the initial dose of desipramine should be markedly reduced. The dose of desipramine can then be adjusted based on clinical response; however, a dose above 40 mg/day is not recommended.

Paroxetine (CYP2D6 inhibitor and substrate):

When the combination dose of dextromethorphan 30 mg/quinidine 30 mg was added to paroxetine at steady state, paroxetine exposure (AUC0-24) increased by 1.7 fold and Cmax increased by 1.5 fold. Consideration should be given to initiating treatment with a lower dose of paroxetine if given with NUEDEXTA. The dose of paroxetine can then be adjusted based on clinical response; however, dosage above 35 mg/day is not recommended.

7.6 Digoxin

Quinidine is an inhibitor of P-glycoprotein. Concomitant administration of quinidine with digoxin, a P-glycoprotein substrate, results in serum digoxin levels that may be as much as doubled. Plasma digoxin concentrations should be closely monitored in patients taking NUEDEXTA concomitantly, and the digoxin dose reduced, as necessary.

7.7 Alcohol

As with any other CNS drug, caution should be used when NUEDEXTA is taken in combination with other centrally acting drugs and alcohol.

8 USE IN SPECIFIC POPULATIONS

8.1 Pregnancy

Risk Summary

There are no adequate data on the developmental risk associated with the use of NUEDEXTA in pregnant women. In oral studies conducted in rats and rabbits, a combination of dextromethorphan/quinidine demonstrated developmental toxicity, including teratogenicity (rabbits) and embryo lethality, when given to pregnant animals (see Data). In the U.S. general population, the estimated background risk of major birth defects and miscarriage in clinically recognized pregnancies is 2-4% and 15-20%, respectively. The estimated background risk of major birth defects and miscarriage for the indicated population is unknown.

Data

Animal Data

When dextromethorphan/quinidine was administered orally (0/0, 5/100, 15/100, and 50/100 mg/kg/day) to pregnant rats during the period of organogenesis, embryo-fetal deaths were observed at the highest dose tested and reduced skeletal ossification was observed at all doses. The lowest dose tested (5/100 mg/kg/day) is approximately 1/50 times the recommended human dose (RHD) of 40/20 mg/day on a mg/m^2 basis. Oral administration to pregnant rabbits during organogenesis in two separate studies (0/0, 5/60, 15/60, and 30/60 mg/kg/day; 0/0, 5/100, 15/100, and 50/100 mg/kg/day) resulted in an increased incidence of fetal malformations at all but the lowest dose tested. The no-effect dose (5/100 mg/kg/day) is approximately 2/100 times the RHD on a mg/m^2 basis.

When dextromethorphan/quinidine was orally administered to female rats during pregnancy and lactation in two separate studies (0/0, 5/100, 15/100, and 30/100 mg/kg/day; 0/0, 5/100, 15/100, and 50/100 mg/kg/day), pup survival and pup weight were decreased at all doses, and developmental delay was observed in offspring at the mid and high doses. A no-effect dose for adverse developmental effects was not identified. The lowest dose tested (5/100 mg/kg/day) is approximately 1/50 times the RHD on a mg/m^2 basis.

When dextromethorphan/quinidine was orally administered (0/0, 5/50, 15/50, 25/50 mg/kg) to male and female rats on Postnatal Day 7, the highest dose resulted in neuronal death in brain (thalamus and medulla oblongata). Postnatal Day 7 in rat corresponds to the third trimester of the gestation through the first several months of life but may extend to approximately three years of age in humans.

8.2 Lactation

Risk Summary

Quinidine is excreted in human milk. It is not known whether dextromethorphan is excreted in human milk. There are no data on the effects of quinidine or dextromethorphan on the breastfed infant or the effects on milk production. The development and health benefits of breastfeeding should be considered along with the mother's clinical need for NUEDEXTA and any potential adverse effects on the breastfed infant from NUEDEXTA or from the underlying material condition.

8.4 Pediatric Use

The safety and effectiveness in pediatric patients below the age of 18 have not been established.

8.5 Geriatric Use

Of the total number of patients with PBA in clinical studies of NUEDEXTA, 14% were 65 years old and over, while 2% were 75 and over. Clinical studies of NUEDEXTA did not include sufficient number of patients aged 65 and over to determine whether they respond differently than younger patients. In general, dose selection for an elderly patient should be cautious, usually starting at the low end of the dosing range, reflecting the greater frequency of decreased hepatic, renal, or cardiac function, and of concomitant disease or other drug therapy.

8.6 Renal Impairment

Dose adjustment of NUEDEXTA is not required in patients with mild to moderate renal impairment [see Clinical Pharmacology (12.3)]. The pharmacokinetics of NUEDEXTA have not been evaluated in patients with severe renal impairment; however, increases in dextromethorphan and/or quinidine levels are likely to be observed.

8.7 Hepatic Impairment

Dose adjustment of NUEDEXTA is not required in patients with mild to moderate hepatic impairment. The pharmacokinetics of NUEDEXTA have not been evaluated in patients with severe hepatic impairment; however, increases in dextromethorphan and/or quinidine levels are likely to be observed.

9 DRUG ABUSE AND DEPENDENCE

NUEDEXTA is a low-affinity uncompetitive NMDA antagonist and sigma-1 receptor agonist that has not been systematically studied in animals or humans for its potential for abuse, tolerance, or physical dependence. However, NUEDEXTA is a combination product containing dextromethorphan and quinidine, and cases of dextromethorphan abuse have been reported, predominantly in adolescents.

While clinical trials did not reveal drug-seeking behavior, these observations were not systematic and it is not possible to predict on the basis of this experience the extent to which NUEDEXTA will be misused, diverted, and/or abused once marketed. Therefore, patients with a history of drug abuse should be observed closely for signs of NUEDEXTA misuse or abuse (e.g., development of tolerance, increases in dose, drug-seeking behavior).

10 OVERDOSAGE

Evaluation and treatment of NUEDEXTA overdose is based on experience with the individual components, dextromethorphan and quinidine. Metabolism of the dextromethorphan component of NUEDEXTA is inhibited by the quinidine component, such that adverse effects of overdose due to NUEDEXTA might be more severe or more persistent compared to overdose of dextromethorphan alone.

During development of NUEDEXTA, dose combinations of dextromethorphan/quinidine containing up to 6-times higher dextromethorphan dose and 12-times higher quinidine dose were studied. The most common adverse events were mild to moderate nausea, dizziness, and headache.

The most important adverse effects of acute quinidine overdose are ventricular arrhythmias and hypotension. Other signs and symptoms of overdose may include vomiting, diarrhea, tinnitus, high-frequency hearing loss, vertigo, blurred vision, diplopia, photophobia, headache, confusion, and delirium.

While therapeutic doses of quinidine for treatment of cardiac arrhythmia or malaria are generally 10-fold, or more, higher than the dose of quinidine in NUEDEXTA, potentially fatal cardiac arrhythmia, including torsades de pointes, can occur at quinidine exposures that are possible from NUEDEXTA overdose.

Adverse effects of dextromethorphan overdose include nausea, vomiting, stupor, coma, respiratory depression, seizures, tachycardia, hyperexcitability, and toxic psychosis. Other adverse effects include ataxia, nystagmus, dystonia, blurred vision, and changes in muscle reflexes. Dextromethorphan may cause serotonin syndrome, and this risk is increased by overdose, particularly if taken with other serotonergic agents, SSRIs or tricyclic antidepressants.

10.1 Treatment of Overdose

While serum quinidine levels can be measured, electrocardiographic monitoring of the QTc interval is a better predictor of quinidine-induced arrhythmia. Treatment of hemodynamically unstable polymorphic ventricular tachycardia (including torsades de pointes) is either immediate cardioversion or, if a cardiac pacemaker is in place or immediately available, immediate overdrive pacing. After pacing or cardioversion, further management must be guided by the length of the QTc interval. Factors contributing to QTc prolongation (especially hypokalemia and hypomagnesemia) should be sought out and (if possible) aggressively corrected. Prevention of recurrent torsades de pointes may require sustained overdrive pacing or the cautious administration of isoproterenol (30 to 150 ng/kg/min).

Because of the theoretical possibility of QT-prolonging effects that might be additive to those of quinidine, other antiarrhythmics with Class I (procainamide) or Class III activities should (if possible) be avoided.

If the post-cardioversion QTc interval is prolonged, then the pre-cardioversion polymorphic ventricular tachyarrhythmia was (by definition) torsades de pointes. In this case, class Ib antiarrhythmics like lidocaine are unlikely to be of value, and other Class I and Class III antiarrhythmics are likely to exacerbate the situation.

Quinidine-induced hypotension that is not due to an arrhythmia is likely to be a consequence of quinidine-related α-blockade and vasorelaxation. Treatment of hypotension should be directed at symptomatic and supportive measures. Repletion of central volume (Trendelenburg positioning, saline infusion) may be sufficient therapy; other interventions reported to have been beneficial in this setting are those that increase peripheral vascular resistance, including α-agonist catecholamines (norepinephrine).

Quinidine:

Adequate studies of orally administered activated charcoal in human overdoses of quinidine have not been reported, but there are animal data showing significant enhancement of systemic elimination following this intervention, and there is at least one human case report in which the elimination half-life of quinidine in the serum was apparently shortened by repeated gastric lavage. Activated charcoal should be avoided if an ileus is present; the conventional dose is 1 g/kg, administered every 2 to 6 hours as a slurry with 8 mL/kg of tap water. Although renal elimination of quinidine might theoretically be accelerated by maneuvers to acidify the urine, such maneuvers are potentially hazardous and of no demonstrated benefit. Quinidine is not usefully removed from the circulation by dialysis. Following quinidine overdose, drugs that delay elimination of quinidine (cimetidine, carbonic anhydrase inhibitors, thiazide diuretics) should be withdrawn unless absolutely required.

Dextromethorphan:

Treatment of dextromethorphan overdosage should be directed at symptomatic and supportive measures.

11 DESCRIPTION

NUEDEXTA is an oral formulation of dextromethorphan hydrobromide USP and quinidine sulfate USP in a fixed dose combination.

Dextromethorphan hydrobromide is the pharmacologically active ingredient of NUEDEXTA that acts on the central nervous system (CNS). The chemical name is dextromethorphan hydrobromide: morphinan, 3-methoxy-17-methyl-, (9α, 13α, 14α), hydrobromide monohydrate. Dextromethorphan hydrobromide has the empirical formula C18H25NO•HBr•H2O with a molecular weight of 370.33. The structural formula is:

Quinidine sulfate is a specific inhibitor of CYP2D6-dependent oxidative metabolism used in NUEDEXTA to increase the systemic bioavailability of dextromethorphan. The chemical name is quinidine sulfate: cinchonan-9-o1, 6'-methoxy-, (9S) sulfate (2:1), (salt), dihydrate. Quinidine sulfate dihydrate has the empirical formula of (C20H24N2O2)2•H2SO4•2H2O with a molecular weight of 782.96. The structural formula is:

The combination product, NUEDEXTA, is a white to off-white powder. NUEDEXTA is available for oral use as NUEDEXTA which contains 20 mg dextromethorphan hydrobromide and 10 mg quinidine sulfate. The active ingredients are dextromethorphan hydrobromide monohydrate USP and quinidine sulfate dihydrate USP. Inactive ingredients in the capsule are croscarmellose sodium NF, microcrystalline cellulose NF, colloidal silicon dioxide NF, lactose monohydrate NF, and magnesium stearate NF.

12 CLINICAL PHARMACOLOGY

12.1 Mechanism of Action

Dextromethorphan (DM) is a sigma-1 receptor agonist and an uncompetitive NMDA receptor antagonist. Quinidine increases plasma levels of dextromethorphan by competitively inhibiting cytochrome P450 2D6, which catalyzes a major biotransformation pathway for dextromethorphan. The mechanism by which dextromethorphan exerts therapeutic effects in patients with pseudobulbar affect is unknown.

12.2 Pharmacodynamics

Cardiac Electrophysiology

The effect of dextromethorphan 30 mg/quinidine 10 mg (for 7 doses) on QTc prolongation was evaluated in a randomized, double-blind (except for moxifloxacin), placebo- and positive-controlled (400 mg moxifloxacin) crossover thorough QT study in 50 fasted normal healthy men and women with CYP2D6 extensive metabolizer (EM) genotype. Mean changes in QTcF were 6.8 ms for dextromethorphan 30 mg/quinidine 10 mg and 9.1 ms for the reference positive control (moxifloxacin). The maximum mean (95% upper confidence bound) difference from placebo after baseline correction was 10.2 (12.6) ms. This test dose is adequate to represent the steady state exposure in patients with CYP2D6 extensive metabolizer phenotype.

The effects of supratherapeutic doses of dextromethorphan/quinidine (30 mg/30 mg and 60 mg/60 mg, for 7 doses) on QTc prolongation was evaluated in a randomized, placebo-controlled, double-blind, crossover design with an additional open-label positive control (400 mg moxifloxacin) arm in 36 healthy volunteers. The maximum mean (95% upper confidence bound) differences from placebo after baseline-correction were 10.2 (14.6) and 18.4 (22.7) ms following dextromethorphan/quinidine doses of 30 mg/30 mg and 60/60 mg, respectively. The supratherapeutic doses are adequate to represent exposure increases due to drug-drug interactions and organ dysfunctions.

12.3 Pharmacokinetics

NUEDEXTA contains dextromethorphan and quinidine, both of which are metabolized primarily by liver enzymes. Quinidine's primary pharmacological action in NUEDEXTA is to competitively inhibit the metabolism of dextromethorphan catalyzed by CYP2D6 in order to increase and prolong plasma concentrations of dextromethorphan [see Warnings and Precautions (5.4, 5.8), and Clinical Pharmacology (12.5)]. Studies were conducted with the individual components of NUEDEXTA in healthy subjects to determine single-dose and multiple-dose kinetics of orally administered dextromethorphan in combination with quinidine. The increase in dextromethorphan levels appeared approximately dose proportional when the dextromethorphan dose was increased from 20 mg to 30 mg in the presence of 10 mg of quinidine.

Absorption

Following single and repeated combination doses of dextromethorphan 30 mg/quinidine 10 mg, dextromethorphan/quinidine-treated subjects had an approximately 20-fold increase in dextromethorphan exposure compared to dextromethorphan given without quinidine.

Following repeated doses of dextromethorphan 30 mg/quinidine 10 mg and dextromethorphan 20 mg/quinidine 10 mg (NUEDEXTA), maximal plasma concentrations (Cmax) of dextromethorphan are reached approximately 3 to 4 hours after dosing and maximal plasma concentrations of quinidine are reached approximately 1 to 2 hours after dosing.

In extensive metabolizers, mean Cmax and AUC0-12 values of dextromethorphan and dextrorphan increased as doses of dextromethorphan increased from 20 to 30 mg; mean Cmax and AUC0-12 values of quinidine appeared similar.

The mean plasma Cmax of quinidine following twice daily co-administration of dextromethorphan 30 mg/quinidine 10 mg in patients with PBA was within 1 to 3% of the concentrations required for antiarrhythmic efficacy (2 to 5 mcg/mL).

NUEDEXTA may be taken without regard to meals as food does not affect the exposure of dextromethorphan and quinidine significantly.

Distribution

After NUEDEXTA administration, protein binding remains essentially the same as that after administration of the individual components; dextromethorphan is approximately 60 to 70% protein bound and quinidine is approximately 80 to 89% protein bound.

Metabolism and Excretion

NUEDEXTA is a combination product containing dextromethorphan and quinidine. Dextromethorphan is metabolized by CYP2D6 and quinidine is metabolized by CYP3A4. After dextromethorphan 30 mg/quinidine 30 mg administration in extensive metabolizers, the elimination half-life of dextromethorphan was approximately 13 hours and the elimination half-life of quinidine was approximately 7 hours.

There are several hydroxylated metabolites of quinidine. The major metabolite of quinidine is 3-hydroxyquinidine. The 3-hydroxymetabolite is considered to be at least half as pharmacologically active as quinidine with respect to cardiac effects such as QT prolongation.

When the urine pH is less than 7, about 20% of administered quinidine appears unchanged in the urine, but this fraction drops to as little as 5% when the urine is more alkaline. Renal clearance involves both glomerular filtration and active tubular secretion, moderated by (pH-dependent) tubular reabsorption.

Specific Populations

Geriatric Use

The pharmacokinetics of dextromethorphan/quinidine have not been investigated systematically in elderly subjects (aged >65 years), although such subjects were included in the clinical program. A population pharmacokinetic analysis of 170 subjects (148 subjects <65 years old and 22 subjects ≥65 years old) administered dextromethorphan 30 mg/quinidine 30 mg revealed similar pharmacokinetics in subjects <65 years and those ≥65 years of age.

Pediatric Use

The pharmacokinetics of NUEDEXTA in pediatric patients have not been studied.

Gender

A population pharmacokinetic analysis based on data from 109 subjects (75 male; 34 female) showed no apparent gender differences in the pharmacokinetics of NUEDEXTA.

Race

A population pharmacokinetic analysis of race with 109 subjects (20 Caucasian; 71 Hispanic; 18 Black) revealed no apparent racial differences in the pharmacokinetics of NUEDEXTA.

Renal Impairment

In a study of a combination dose of dextromethorphan 30 mg/quinidine 30 mg TWICE DAILY in 12 subjects with mild (CLCR 50 to 80 mL/min) or moderate (CLCR 30 to 50 mL/min) renal impairment (6 each) compared to 9 healthy subjects (matched in gender, age, and weight range to impaired subjects), subjects showed little difference in quinidine or dextromethorphan pharmacokinetics compared to healthy subjects. Dose adjustment is, therefore, not required in mild or moderate renal impairment. NUEDEXTA has not been studied in patients with severe renal impairment.

Hepatic Impairment

In a study of a combination dose of dextromethorphan 30 mg/quinidine 30 mg TWICE DAILY in 12 subjects with mild or moderate hepatic impairment (as indicated by the Child-Pugh method; 6 each) compared to 9 healthy subjects (matched in gender, age, and weight range to impaired subjects), subjects with moderate hepatic impairment showed similar dextromethorphan AUC and Cmax and clearance compared to healthy subjects. Mild to moderate hepatic impairment had little effect on quinidine pharmacokinetics. Patients with moderate impairment showed an increased frequency of adverse events. Therefore, dosage adjustment is not required in patients with mild and moderate hepatic impairment, although additional monitoring for adverse reactions should be considered. Quinidine clearance is unaffected by hepatic cirrhosis, although there is an increased volume of distribution that leads to an increase in the elimination half-life. Neither dextromethorphan alone nor NUEDEXTA has been evaluated in patients with severe hepatic impairment.

12.4 Drug-Drug Interactions

The potential for dextromethorphan and quinidine to inhibit or induce cytochrome P450 in vitro were evaluated in human microsomes. Dextromethorphan did not inhibit (<20% inhibition) any of the tested isoenzymes: CYP1A2, CYP2A6, CYP2B6, CYP2C8, CYP2C9, CYP2C19, CYP2D6, CYP2E1, or CYP3A4 in human liver microsomes at concentrations up to 5 microM. Quinidine did not inhibit (<30% inhibition) CYP1A2, CYP2A6, CYP2B6, CYP2C8, CYP2C9, CYP2C19, CYP2E1, or CYP3A4 in human microsomes at concentrations up to 5 microM. Quinidine inhibited CYP2D6 with a half maximal inhibitory concentration (IC50) of less than 0.05 microM. Neither dextromethorphan nor quinidine induced CYP1A2, CYP2B6 or CYP3A4 in human hepatocytes at concentrations up to 4.8 microM.

Desipramine (CYP2D6 substrate)

Co-administration of dextromethorphan 30 mg/quinidine 30 mg with the tricyclic antidepressant desipramine, a CYP2D6 substrate, when desipramine was given at a dose of 25 mg once daily in 13 healthy volunteers resulted in an approximately 8-fold increase in steady state desipramine exposure (Cmin) compared to desipramine given alone. Therefore, concomitant administration of NUEDEXTA and drugs undergoing CYP2D6 metabolism should be evaluated for appropriate dose adjustment or alternative medication if the concomitant medication depends primarily on CYP2D6 metabolism and has a narrow therapeutic index, or if it relies on CYP2D6 for conversion to an active species [see Warnings and Precautions (5.4)].

Paroxetine (CYP2D6 inhibitor and substrate)

Co-administration of the selective serotonin reuptake inhibitor paroxetine and a higher combination dose of dextromethorphan/quinidine (dextromethorphan 30 mg/quinidine 30 mg) was studied in 27 healthy volunteers. Group 1 (N = 14) received paroxetine 20 mg once daily for 12 days followed by the addition of dextromethorphan 30 mg/quinidine 30 mg twice daily for 8 days. Group 2 (N = 13) received dextromethorphan 30 mg/quinidine 30 mg twice daily for 8 days followed by the addition of paroxetine 20 mg once daily for 12 days. Dextromethorphan exposure (AUC0-12) and Cmax increased by 1.5 fold and 1.4 fold, respectively, and quinidine exposure (AUC0-12) and Cmax increased by 1.4 fold and 1.3 fold, respectively, and dextrorphan exposure (AUC0-12) and Cmax decreased by 14% and 18%, respectively, and paroxetine exposure (AUC0-24) and Cmax increased by 2.3 fold and 2.0 fold, respectively, when paroxetine was added to the combination dose of dextromethorphan/quinidine at steady state (Group 2).

When the combination dose of dextromethorphan/quinidine was added to paroxetine at steady state (Group 1), paroxetine exposure (AUC0-24) and Cmax increased by 1.7 fold and 1.5 fold, respectively, while dextromethorphan and quinidine exposure did not change significantly and dextrorphan exposure (AUC0-12) and Cmax decreased by 34% and 33%, respectively.

Based on these results, when NUEDEXTA is prescribed with drugs such as paroxetine that inhibit or are extensively metabolized by CYP2D6, consideration should be given to initiating treatment with a lower dose. The dose of paroxetine can then be adjusted based on clinical response; however, dosage above 35 mg/day is not recommended [see Warnings and Precautions (5.4)].

NMDA receptor antagonists (memantine)

A drug interaction study was conducted between a higher combination dose of dextromethorphan/quinidine (dextromethorphan 30 mg/quinidine 30 mg) and memantine 20 mg/day to investigate the pharmacokinetic and pharmacodynamic interactions in 52 healthy subjects. Both dextromethorphan and memantine are antagonists of the N-methyl-D-aspartate (NMDA) receptor, which could theoretically result in an additive effect at NMDA receptors and potentially an increased incidence of adverse events. There was no significant difference in the plasma concentrations of dextromethorphan and dextrorphan before and after the administration of memantine. Plasma concentrations of quinidine increased 20 to 30% when memantine was added to dextromethorphan 30 mg/quinidine 30 mg.

12.5 Pharmacogenomics

The quinidine component of NUEDEXTA is intended to inhibit CYP2D6 so that higher exposure to dextromethorphan can be achieved compared to when dextromethorphan is given alone. Approximately 7 to 10% of Caucasians and 3 to 8% of African Americans generally lack the capacity to metabolize CYP2D6 substrates and are classified as PMs. The quinidine component of NUEDEXTA is not expected to contribute to the effectiveness of NUEDEXTA in PMs, but adverse events of the quinidine are still possible. In those patients who may be at risk of significant toxicity due to quinidine, genotyping to determine if they are PMs should be considered prior to making the decision to treat with NUEDEXTA [see Warnings and Precautions (5.4, 5.8), and Clinical Pharmacology (12.3)].

13 NONCLINICAL TOXICOLOGY

13.1 Carcinogenesis, Mutagenesis, Impairment of Fertility

Carcinogenesis

In a 26-week carcinogenicity study in the Tg.rasH2 transgenic mouse, dextromethorphan and quinidine, alone and in combination, at oral doses up to 100/100 mg/kg/day did not show any evidence of carcinogenic potential.

In a two-year carcinogenicity study in rats, dextromethorphan/quinidine were administered at oral doses of 0/0, 5/100, 20/100, 50/100, 50/0, 0/100 mg/kg/day. No biologically significant tumor findings were observed. The highest dose tested (50/100 mg/kg/day) is approximately 12/50 times the maximum recommended human dose (MRHD) of 40/20 mg/day on a mg/m^2 basis.

Mutagenesis

Dextromethorphan/quinidine was negative in an in vitro chromosomal aberration assay in human lymphocytes.

Dextromethorphan was negative in in vitro (bacterial reverse mutation, chromosomal aberration in human lymphocytes) and in vivo (mouse micronucleus) assays.

Quinidine was negative in an in vitro bacterial reverse mutation assay and in an in vivo mouse micronucleus assay. Quinidine induced chromosomal aberrations in an in vitro chromosomal aberration assay in the presence of metabolic activation.

Impairment of fertility

When dextromethorphan/quinidine was administered orally (0/0, 5/100, 15/100, and 50/100 mg/kg/day) to male and female rats prior to and during mating, and continuing to Day 7 of gestation in females, no effect on fertility was observed up to the highest dose tested, which is approximately 12/50 times the MRHD on a mg/m^2 basis.

14 CLINICAL STUDIES

The efficacy of NUEDEXTA was demonstrated in one trial in patients with pseudobulbar affect (PBA). These patients had underlying amyotrophic lateral sclerosis (ALS) or multiple sclerosis (MS). Other trials at higher doses (dextromethorphan 30 mg/quinidine 30 mg) provided supportive evidence.

In the NUEDEXTA trial, patients with PBA were randomized to receive NUEDEXTA dextromethorphan 20 mg/quinidine 10 mg, (N=107), dextromethorphan 30 mg/quinidine 10 mg (N=110), or placebo (N=109) for 12 weeks.

The primary outcome measure, laughing and crying episodes (Figure 1), was statistically significantly lower in each dextromethorphan/quinidine arm compared to placebo, based on an analysis of the sums of the episode counts over the double-blind phase. The secondary endpoint was the Center for Neurologic Studies Lability Scale (CNS-LS), a seven-item self-report questionnaire with 3 items assessing crying and 4 assessing laughter. CNS-LS was analyzed based on the difference between the mean scores on Day 84 and baseline, and was also statistically significantly lower in each dextromethorphan/quinidine arm compared to placebo (Figure 2). There were no clinically important differences between NUEDEXTA and the dextromethorphan 30 mg/quinidine 10 mg arm.

Figure 1: Mean PBA Episode Rates by Visit

Figure 2: Least Square Mean CNS-LS Scores by Visit

Two additional studies conducted using a higher dose combination of dextromethorphan/quinidine (dextromethorphan 30 mg/quinidine 30 mg) provided supportive evidence of NUEDEXTA efficacy. The first was a 4-week study in PBA patients with underlying ALS, and the second was a 12-week study in patients with underlying MS. In both studies, the primary outcome measure, CNS-LS, and the secondary outcome measure, laughing and crying episodes, were statistically significantly decreased by the dextromethorphan/quinidine combination.

16 HOW SUPPLIED/STORAGE AND HANDLING

NUEDEXTA is supplied as brick red gelatin capsules imprinted with "DMQ 20-10". NUEDEXTA is supplied in the following package configuration:

Package Configuration | Capsule Strength (mg) | NDC Code
Bottles of 60 (30 day supply) | dextromethorphan 20 mg/quinidine 10 mg | 59148-053-16

Storage

Store NUEDEXTA capsules at controlled room temperature, 25°C (77°F); excursions permitted to 15°C to 30°C (59°F to 86°F) [see USP Controlled Room Temperature].

17 PATIENT COUNSELING INFORMATION

Hypersensitivity

Patients should be advised a hypersensitivity reaction to NUEDEXTA could occur. Patients should be instructed to seek medical attention immediately if they experience symptoms indicative of hypersensitivity after taking NUEDEXTA [see Contraindications (4.2), Warnings and Precautions (5.1)].

Cardiac effects

Patients should be advised to consult their healthcare provider immediately if they feel faint or lose consciousness. Patients should be counseled to inform their healthcare provider if they have any personal or family history of QTc prolongation [see Contraindications (4.4), Warnings and Precautions (5.3), Drug Interactions (7)].

Dizziness

Patients should be advised that NUEDEXTA may cause dizziness. Precautions to reduce the risk of falls should be taken, particularly for patients with motor impairment affecting gait or a history of falls [see Warnings and Precautions (5.5), Adverse Reactions (6.1)].

Drug Interactions

Inform patients that NUEDEXTA increases the risk of adverse drug interactions. Instruct patients to inform their healthcare provider about all the medications that they are taking before taking NUEDEXTA. Before taking any new medications, patients should tell their healthcare provider that they are taking NUEDEXTA [see Drug Interactions (7)].

Dosing Instructions

Instruct patients to take NUEDEXTA exactly as prescribed. Instruct patients not to take more than 2 capsules in a 24-hour period and to make sure that there is an approximate 12-hour interval between doses, and not to take a double dose after they miss a dose [see Dosage and Administration (2.1)].

General

Patients should not share or give NUEDEXTA to others, even if they have the same symptoms, because it may harm them.

Advise patients to contact their healthcare provider if their PBA symptoms persist or worsen.

Advise patients to keep this and all medications out of reach of children and pets.

Distributed and Marketed by Otsuka America Pharmaceutical, Inc., Rockville, MD 20850 USA

NUEDEXTA is a registered trademark of Avanir Pharmaceuticals, Inc. used under license by Otsuka America Pharmaceutical, Inc.

PRINCIPAL DISPLAY PANEL - 60 Capsule Bottle Label

NDC 59148-053-16

Rx only

60 capsules

NUEDEXTA®

(dextromethorphan HBr and
quinidine sulfate) capsules

20 mg/10 mg